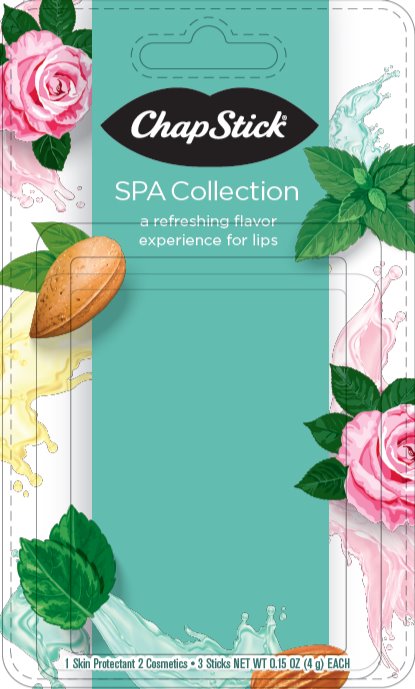 DRUG LABEL: Chapstick
NDC: 0573-2062 | Form: KIT | Route: TOPICAL
Manufacturer: GlaxoSmithKline Consumer Healthcare Holdings (US) LLC
Category: otc | Type: HUMAN OTC DRUG LABEL
Date: 20210324

ACTIVE INGREDIENTS: PETROLATUM 450 mg/1 g
INACTIVE INGREDIENTS: ARACHIDYL PROPIONATE; FD&C BLUE NO. 1--ALUMINUM LAKE; CARNAUBA WAX; CETYL ALCOHOL; ISOPROPYL MYRISTATE; LANOLIN; LIGHT MINERAL OIL; MALTOL; OCTYLDODECANOL; PARAFFIN; PHENYL TRIMETHICONE; SACCHARIN; WHITE WAX; FD&C YELLOW NO. 5; ALUMINUM OXIDE

Drug Facts

ChapStick Mint Tea

Active Ingredients

White Petrolatum 45%

Purpose

Skin Protectant

Uses

- helps prevent and temporarily protects chafed, chapped or cracked lips
- helps prevent and protect from the drying effects of wind and cold weather

Warnings

For external use only

Keep Out of Reach of Children

If swallowed, get medical help or contact a Poison Control Center right away.

Directions

apply as needed

Other information

store at 20-25°C (68-77°F)

Inactive ingredients

arachidyl propionate, blue 1 lake, carnauba wax, cetyl alcohol, isopropyl lanolate, isopropyl myristate, lanolin, light mineral oil, maltol, natural and artificial flavor, octyldodecanol, paraffin, phenyl trimethicone, saccharin, white wax, yellow 5 lake

Questions or comments?

Call weekdays from 9 AM to 5 PM EST at 1-877-227-3421

ChapStick Rose Water

Ingredients

petrolatum, paraffin, mineral oil, octyldodecanol, bis-diglyceryl polyacyladipate-2, caprylic/capric triglyceride, arachidyl propionate, phenyl trimethicone, beeswax, copernicia cerifera (carnauba) wax, isopropyl myristate, cetyl alcohol, lecithin (soy), flavor, saccharin, lanolin, titanium dioxide, red 6 lake, yellow 6 lake, yellow 10 lake

Other information

store at 20-25°C (68-77°F)

Chapstick Almond Oil

Ingredients

petrolatum, paraffin, mineral oil, octyldodecanol, canola oil, bis-diglyceryl polyacyladipate-2, arachidyl propionate, phenyl trimethicone, beeswax, copernicia cerifera (carnauba) wax, isopropyl myristate, cetyl alcohol, lecithin (soy), titanium dioxide, synthetic wax, flavor, saccharin, iron oxides, isopropyl titanium trisostearate, yellow 6 lake

Other information

store at 20-25°C (68-77°F)

Additional information

Paraben-Free

Distributed by: GSK Consumer Healthcare, Warren, NJ 07059

For most recent product information, visit www.chapstick.com

Trademarks owned or licensed by GSK

©2020 GSK or licensor

Principal Display Panel

0573-2062-01

ChapStick®

SPA Collection

a refreshing flavor experience for lips

1 Skin Protectant 2 Cosmetics ·3 Sticks NET WT 0.15 OZ (4 g) EACH

PAA159505